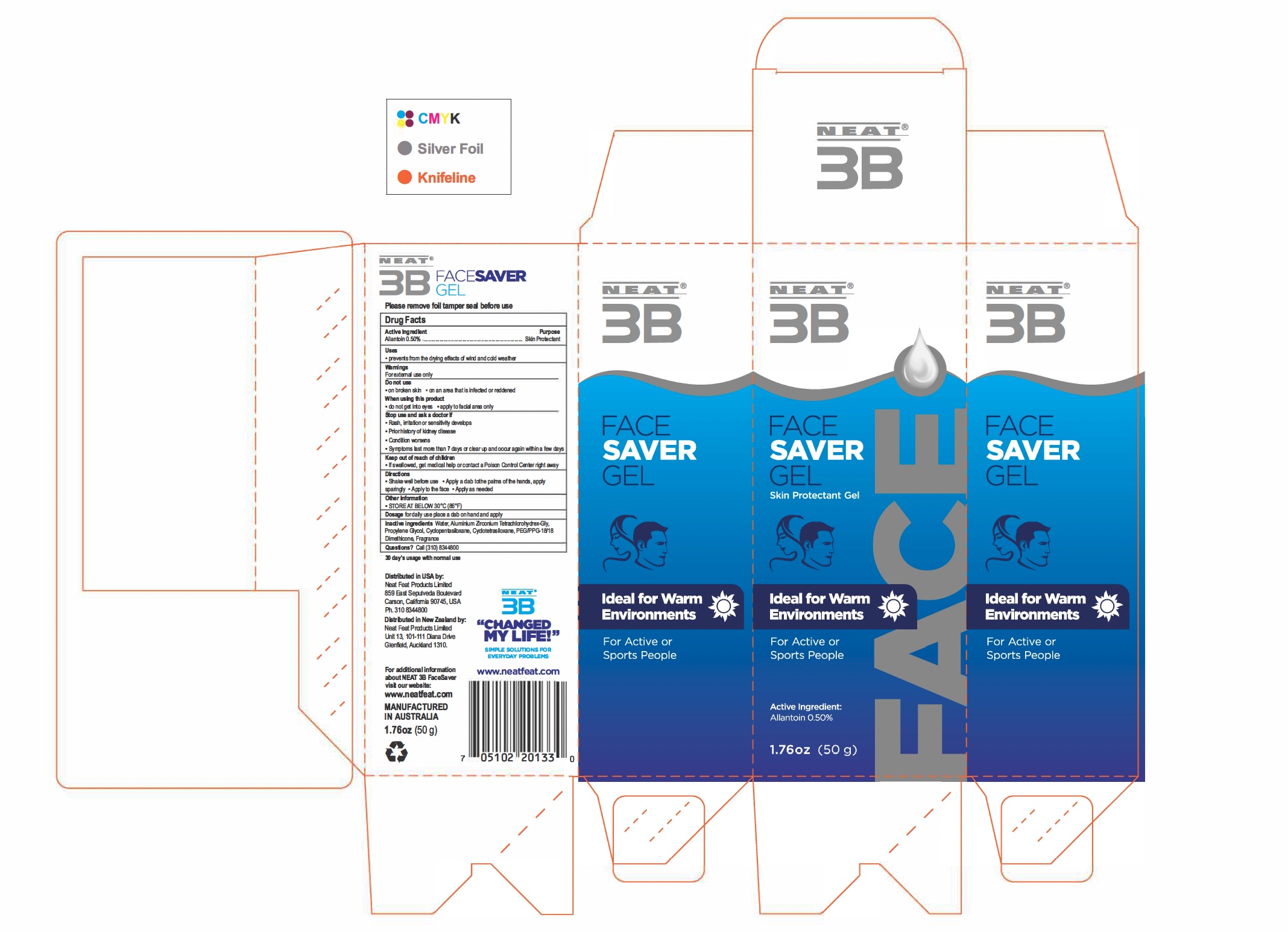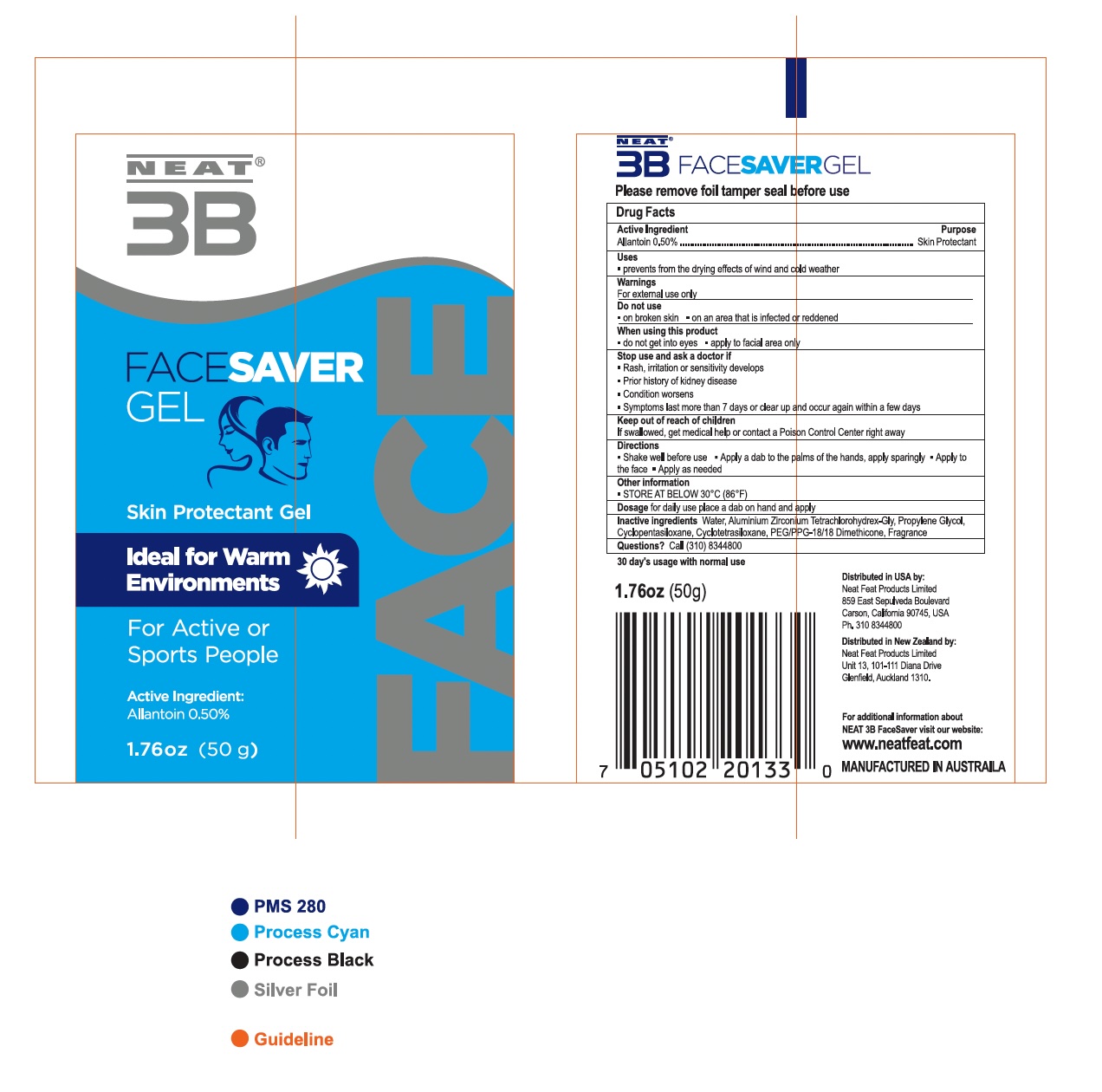 DRUG LABEL: Face Saver Gel
NDC: 50017-034 | Form: GEL
Manufacturer: Neat Feat Products Limited
Category: otc | Type: HUMAN OTC DRUG LABEL
Date: 20250327

ACTIVE INGREDIENTS: ALLANTOIN 0.25 g/50 g
INACTIVE INGREDIENTS: PEG/PPG-18/18 DIMETHICONE; ALUMINUM ZIRCONIUM TRICHLOROHYDREX GLY; CYCLOPENTASILOXANE; PROPYLENE GLYCOL; CYCLOTETRASILOXANE; WATER

FACE SAVER GEL - Skin Protectant Gel

Active Ingredient

Allantoin 0.50%

Purpose

Skin Protectant

INDICATIONS AND USAGE

prevents from the drying effects of wind and cold weather

WARNINGS

For external use only

Do not use

- on broken skin
- on an area that is infected or reddened

When Using this porduct

- do not get into eyes
- apply to facial area only

Stop use and ask a doctor if

- Rash, irritation or sensitivity develops
- Prior history of kidney disease
- Condition worsens
- Symptoms last more than 7 days or clear up and occur again within a few days

Keep out of reach of children

If swallowed, get medical help or contact a Poison Control Center right away

Directions

- Shake well before use
- Apply a dab to the palms of the hands, apply sparingly
- Apply to the face
- Apply as needed

Other Information

STORE AT BELOW 30ºC (86ºF)

Dosage

for daily use place a dab on hand and apply

Inactive Ingredients

Water, Aluminium Zirconium Tetrachlorohydrex-Gly, Propylene Glycol, Cyclopentasiloxane, Cylotetrasiloxane, PEG/PPG-18/18 Dimethicone, Fragrance

Questions?

Call (310)8344800

50 g Tube Box

NEAT

3B

FACE SAVER GEL

Skin Protectant

Ideal for Warm Environments

For Active or sports people